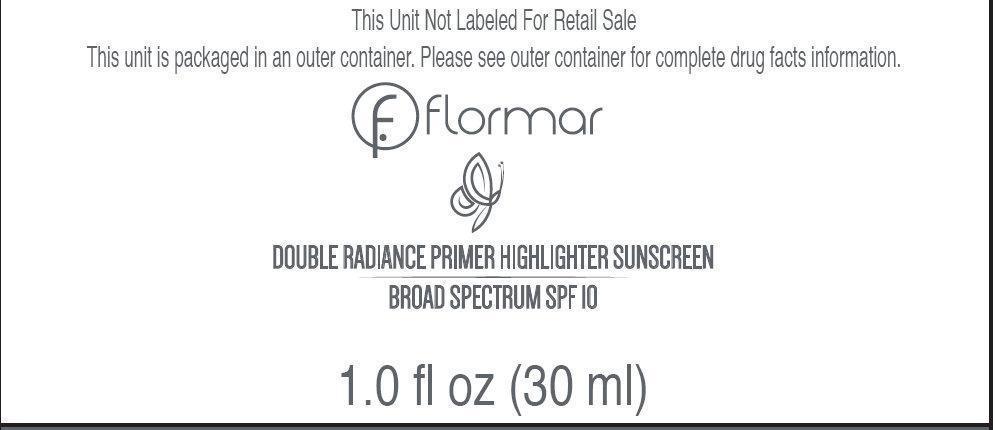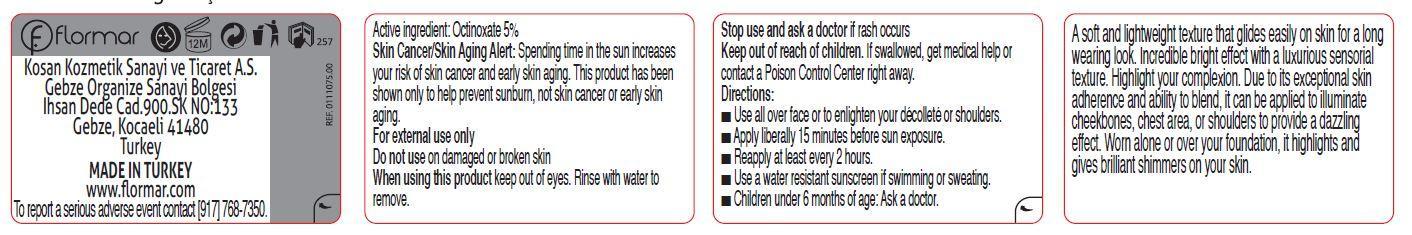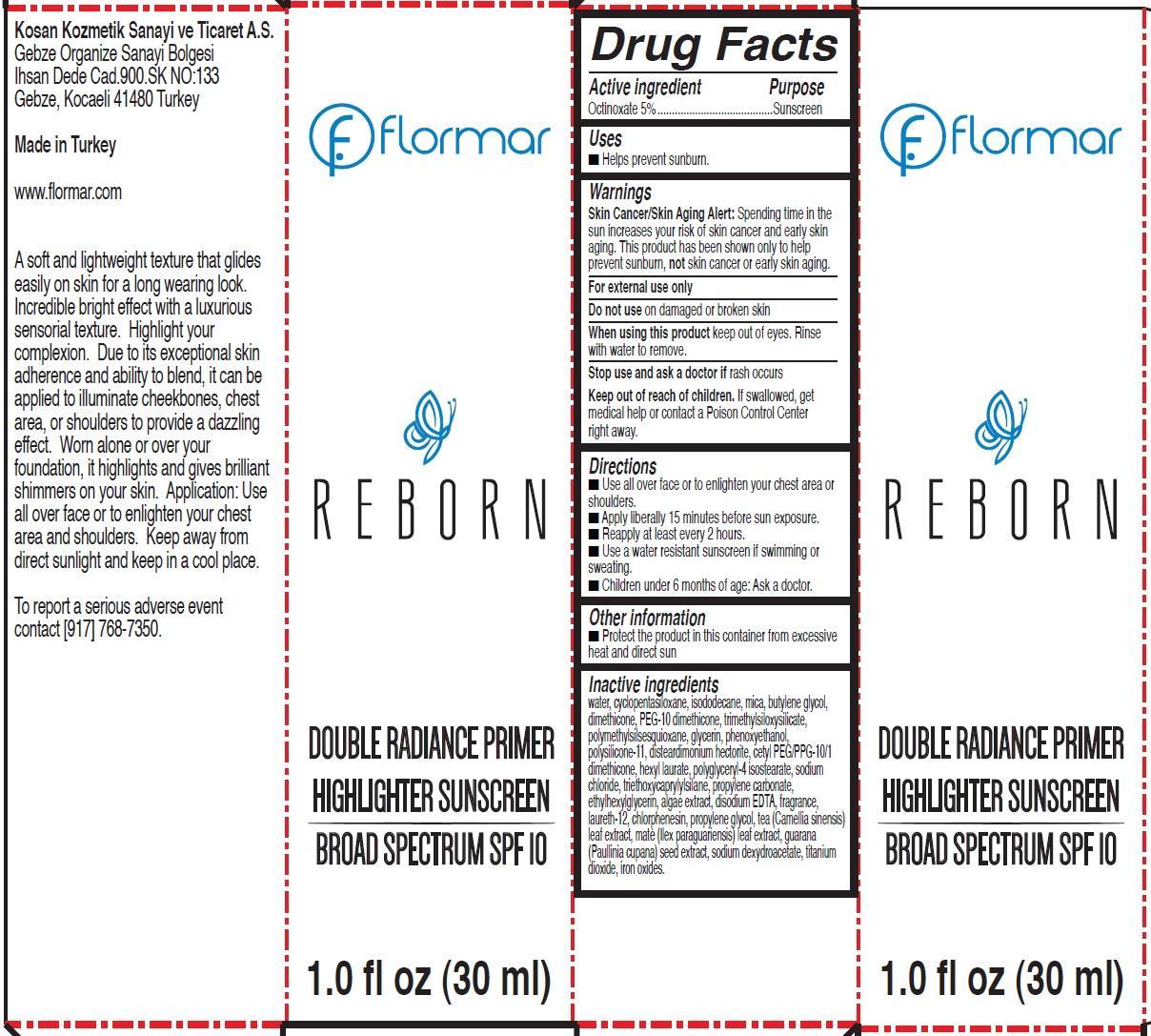 DRUG LABEL: flormar REBORN DOUBLE RADIANCE PRIMER HIGHLIGHTER SUNSCREEN BROAD SPECTRUM SPF 10
NDC: 61722-023 | Form: CREAM
Manufacturer: Kosan Kozmetik Sanayi ve Ticaret A.S.
Category: otc | Type: HUMAN OTC DRUG LABEL
Date: 20191018

ACTIVE INGREDIENTS: OCTINOXATE 50 mg/1 mL
INACTIVE INGREDIENTS: WATER; CYCLOMETHICONE 5; ISODODECANE; MICA; BUTYLENE GLYCOL; DIMETHICONE; GLYCERIN; PHENOXYETHANOL; DISTEARDIMONIUM HECTORITE; HEXYL LAURATE; POLYGLYCERYL-4 ISOSTEARATE; SODIUM CHLORIDE; TRIETHOXYCAPRYLYLSILANE; PROPYLENE CARBONATE; ETHYLHEXYLGLYCERIN; EDETATE DISODIUM; LAURETH-12; CHLORPHENESIN; PROPYLENE GLYCOL; GREEN TEA LEAF; ILEX PARAGUARIENSIS LEAF; PAULLINIA CUPANA SEED; TITANIUM DIOXIDE; FERRIC OXIDE RED

flormar REBORN DOUBLE RADIANCE PRIMER HIGHLIGHTER SUNSCREEN BROAD SPECTRUM SPF 10

Active ingredient

Octinoxate 5%

Purpose

Sunscreen

Uses

- Helps prevent sunburn.

Warnings

Skin Cancer/Skin Aging Alert: Spending time in the sun increases your risk of skin cancer and early skin aging. This product has been shown only to help prevent sunburn, not skin cancer or early skin aging.
For external use only

Do not use

on damaged or broken skin

When using this product

keep out of eyes. Rinse with water to remove.

Stop use and ask a doctor if

rash occurs

Keep out of reach of children.

If swallowed, get medical help or contact a Poison Control Center right away.

Directions

- Use all over face or to enlighten your chest area or shoulders.
- Apply liberally 15 minutes before sun exposure.
- Reapply at least every 2 hours.
- Use a water resistant sunscreen if swimming or sweating.
- Children under 6 months of age: Ask a doctor.

Other information

- Protect the product in this container from excessive heat and direct sun

Inactive ingredients

water, cyclopentasiloxane, isododecane, mica, butylene glycol, dimethicone, PEG-10 dimethicone, trimethylsiloxysilicate, polymethylsilsesquioxane, glycerin, phenoxyethanol, polysilicone-11, disteardimonium hectorite, cetyl PEG/PPG-10/1 dimethicone, hexyl laurate, polyglyceryl-4 isostearate, sodium chloride, triethoxycaprylylsilane, propylene carbonate, ethylhexylglycerin, algae extract, disodium EDTA, fragrance, laureth-12, chlorphenesin, propylene glycol, tea (Camellia sinensis) leaf extract, maté (Ilex paraguariensis) leaf extract, guarana (Paullinia cupana) seed extract, sodium dexydroacetate, titanium dioxide, iron oxides.